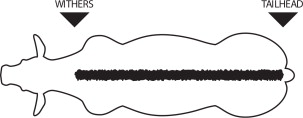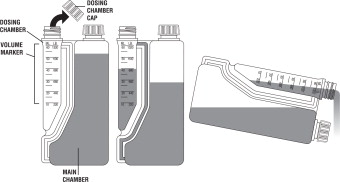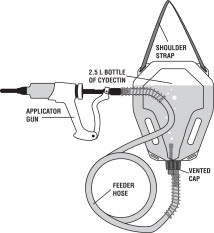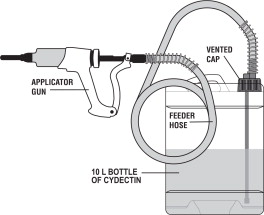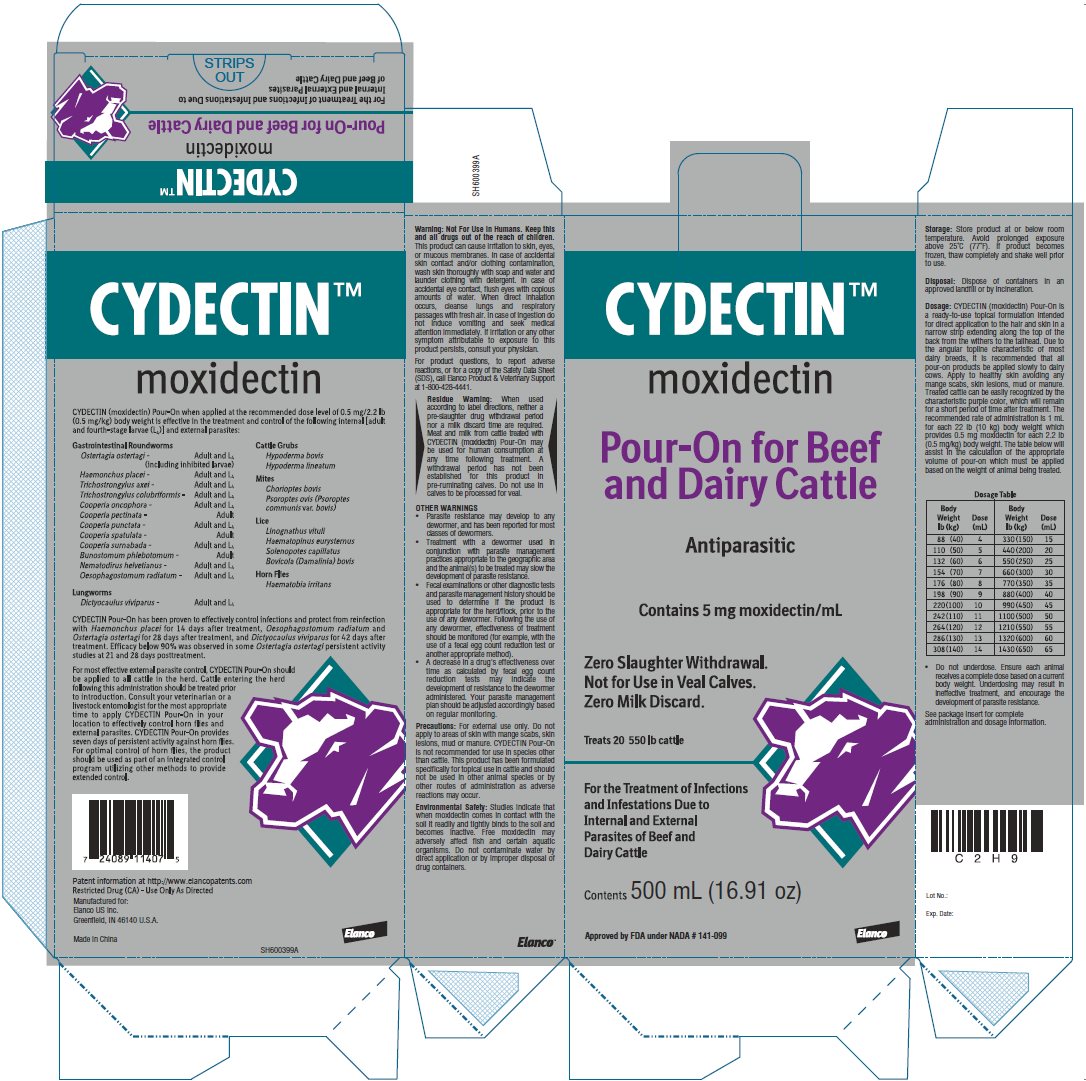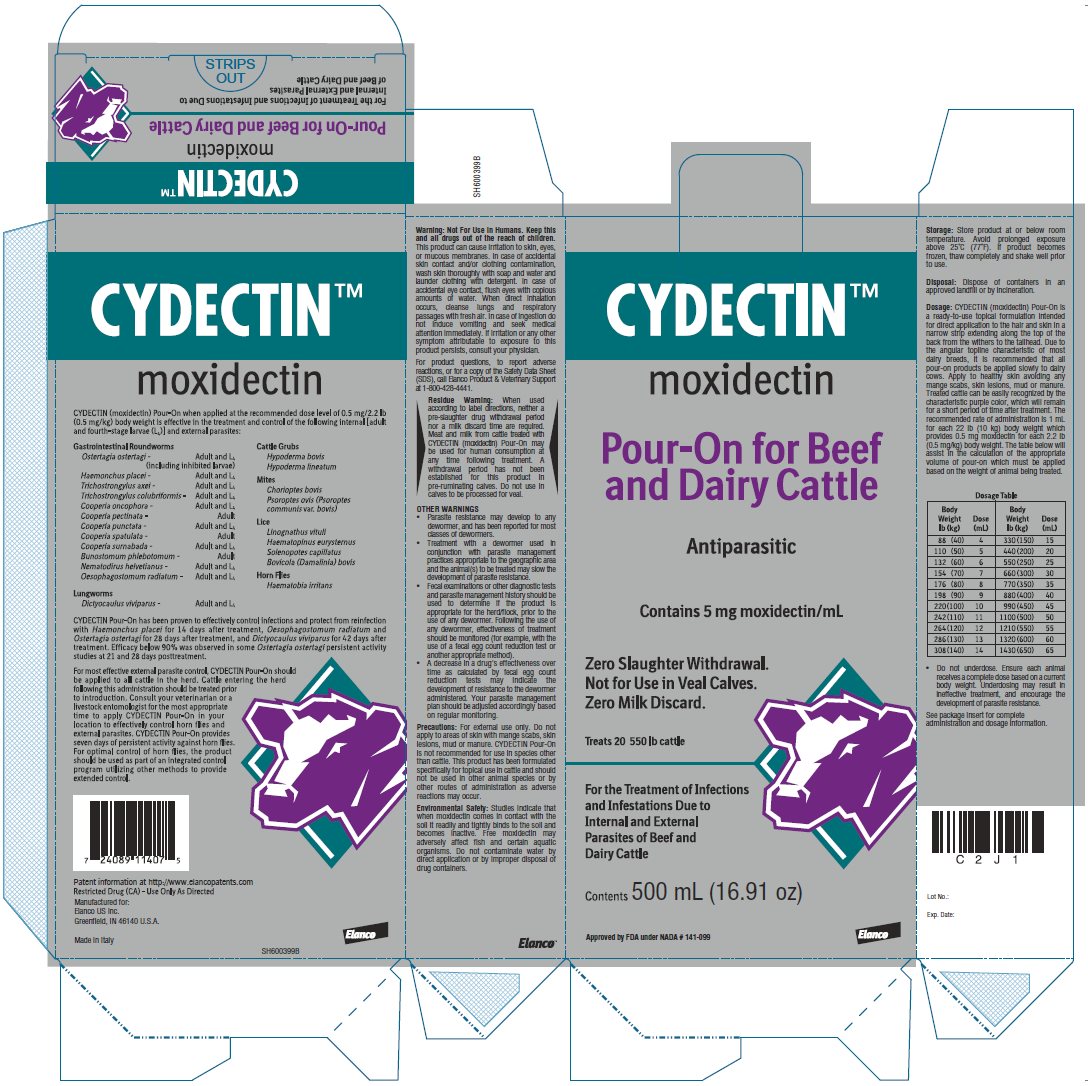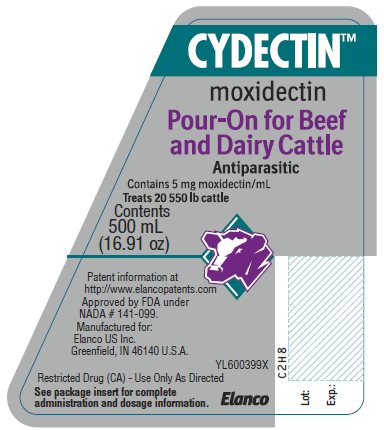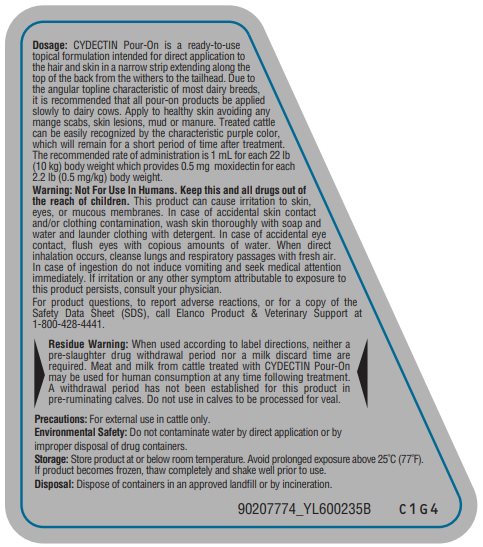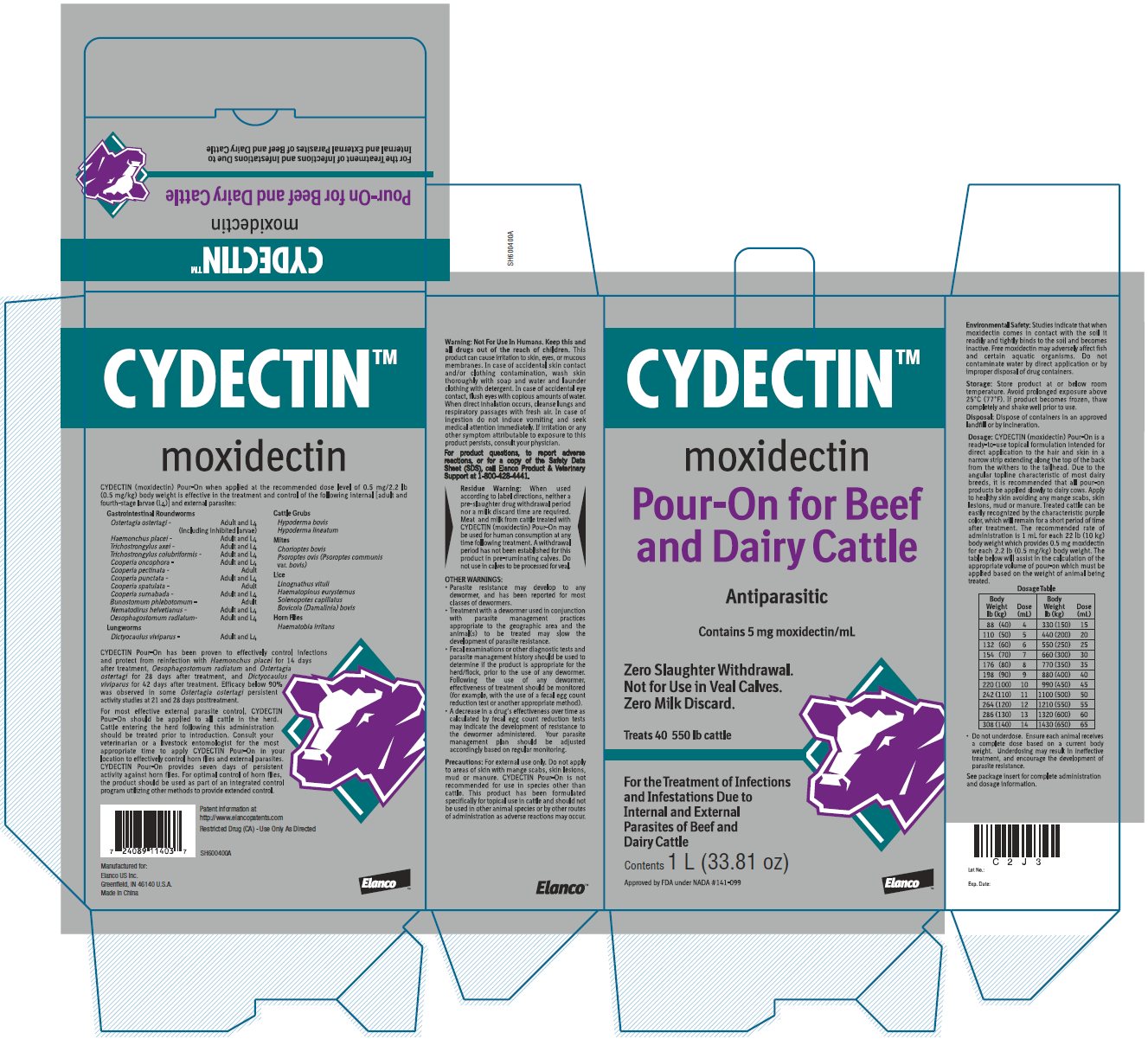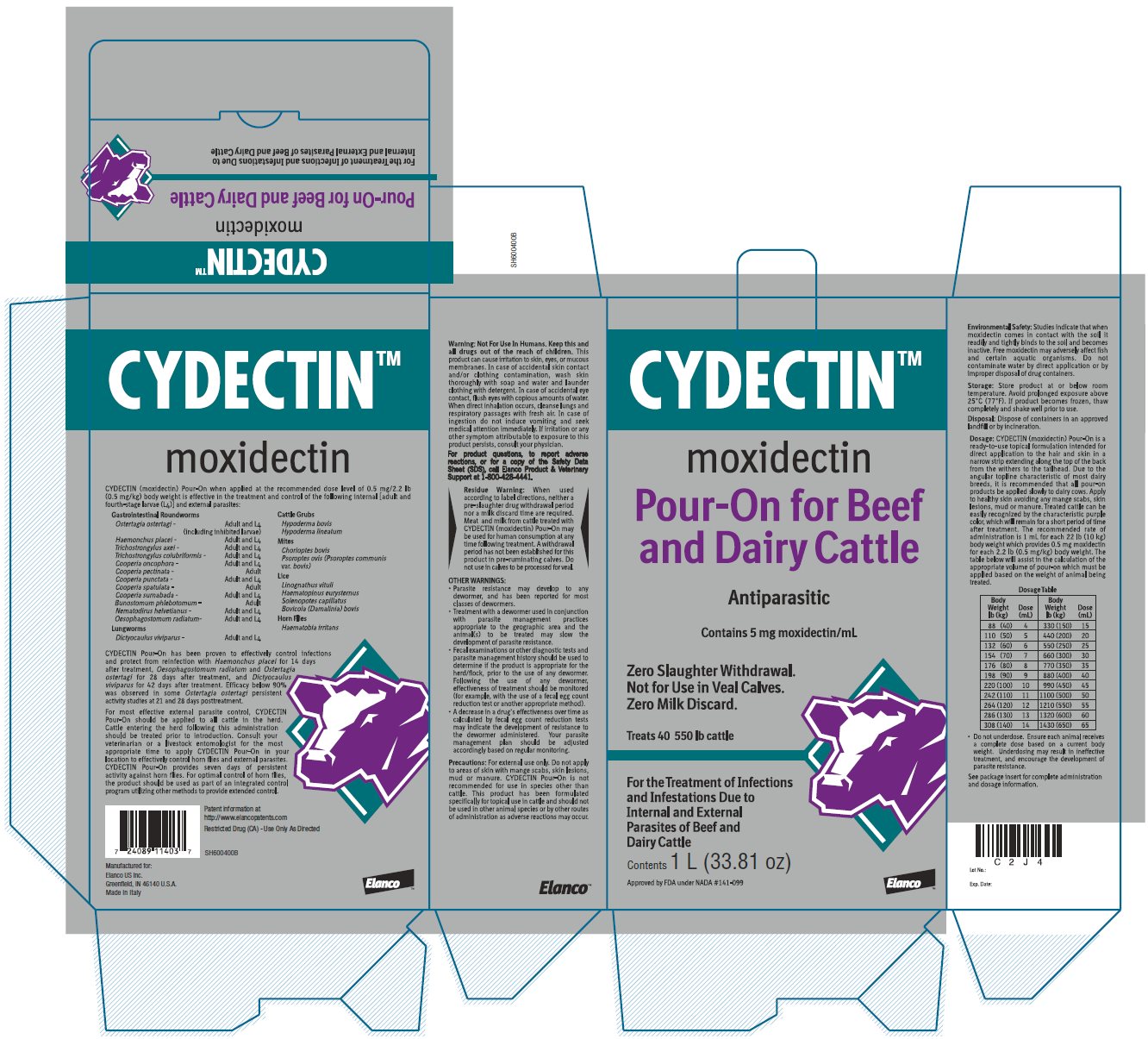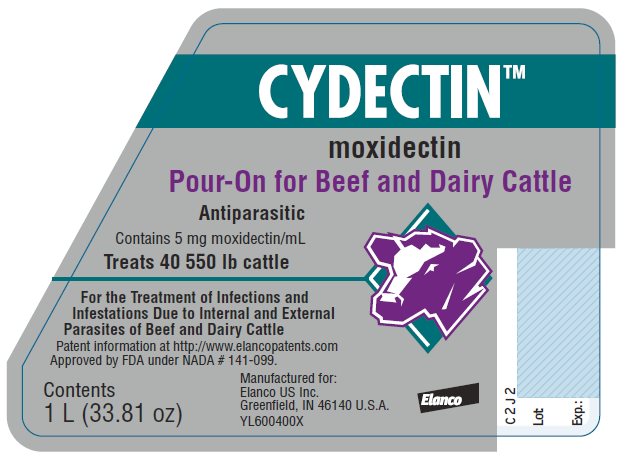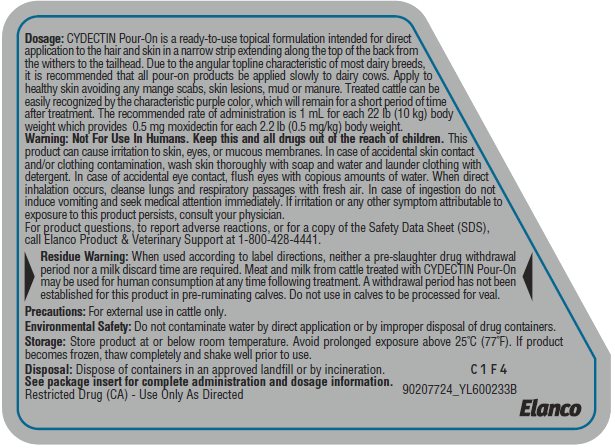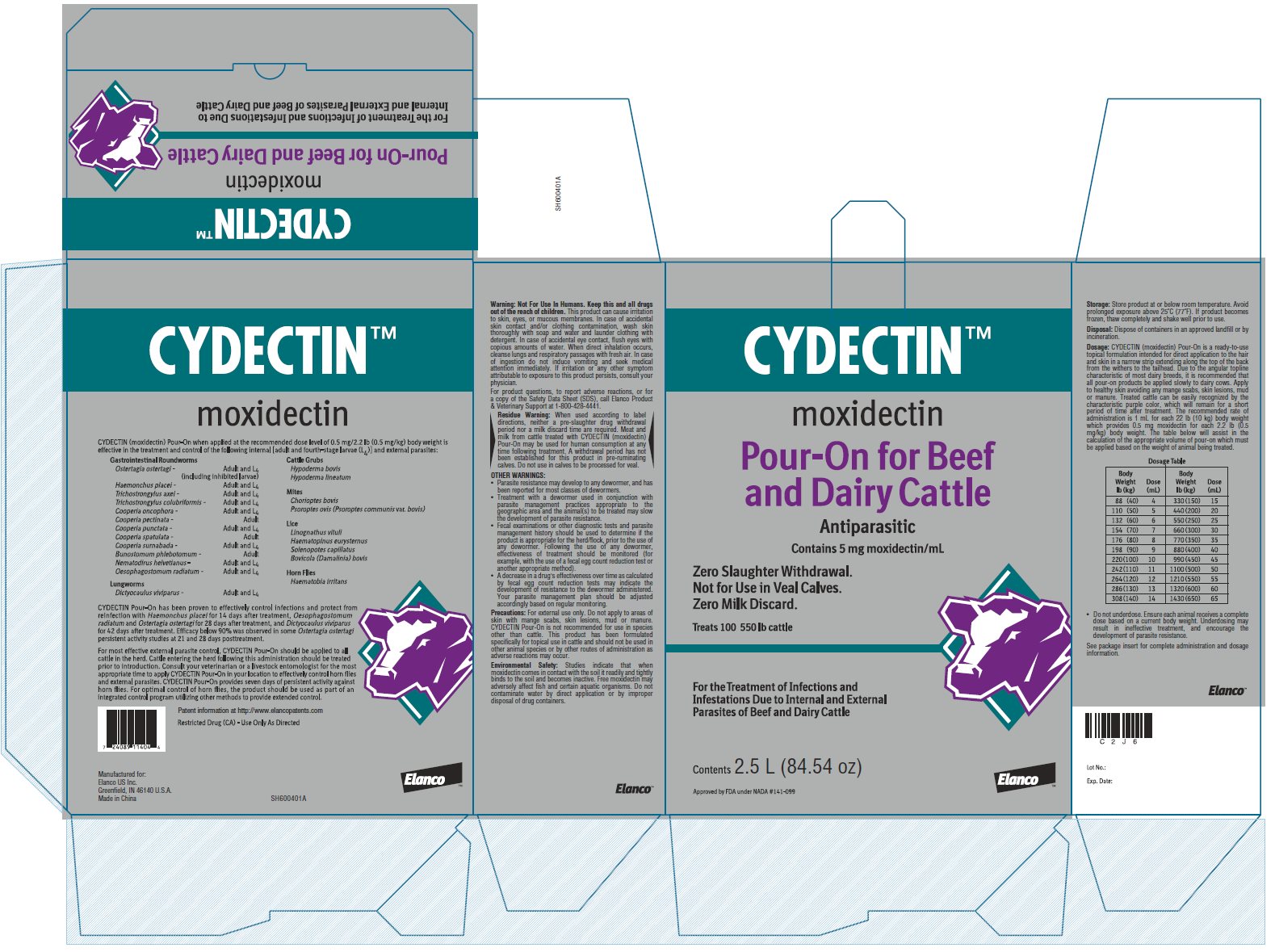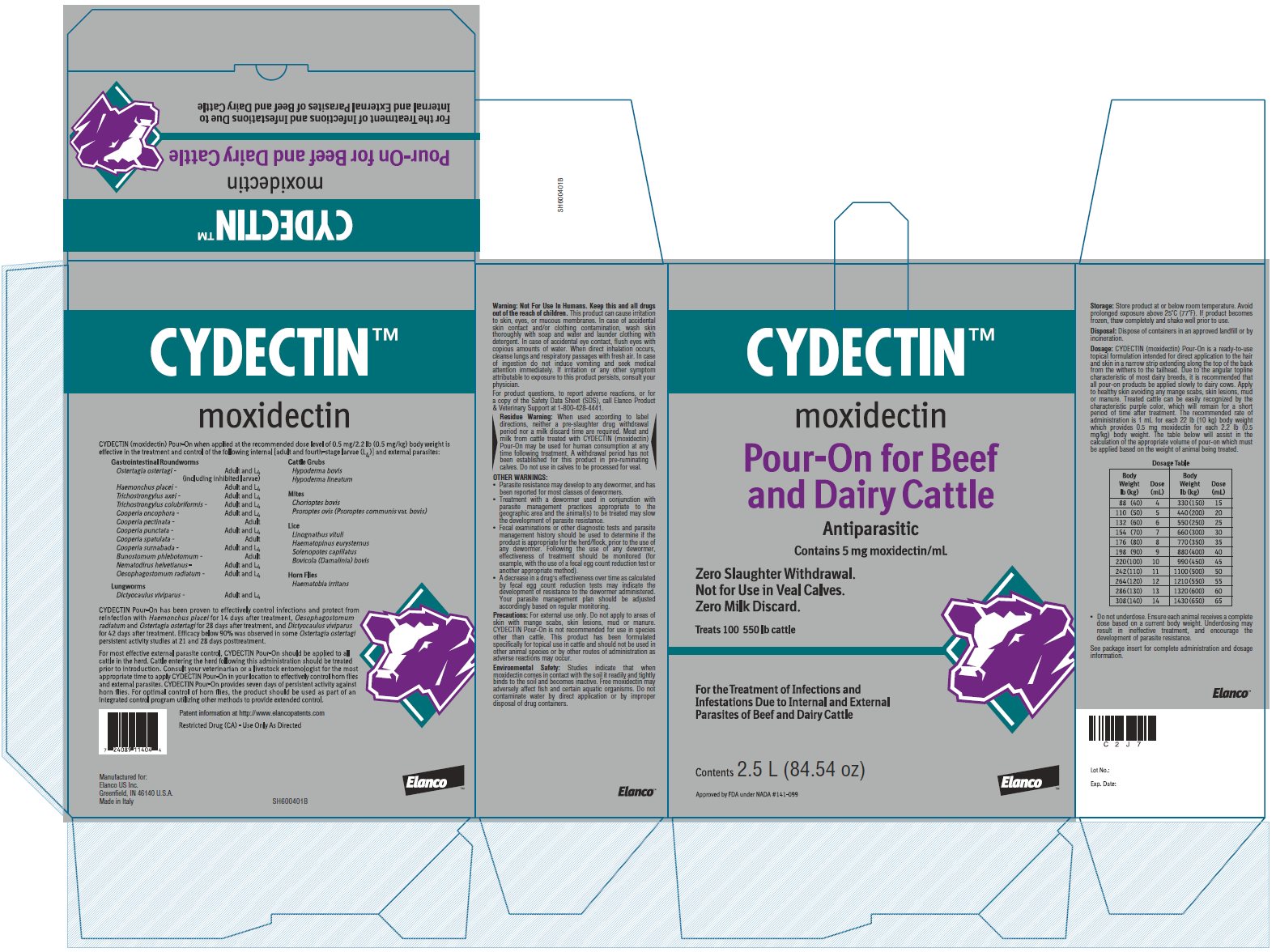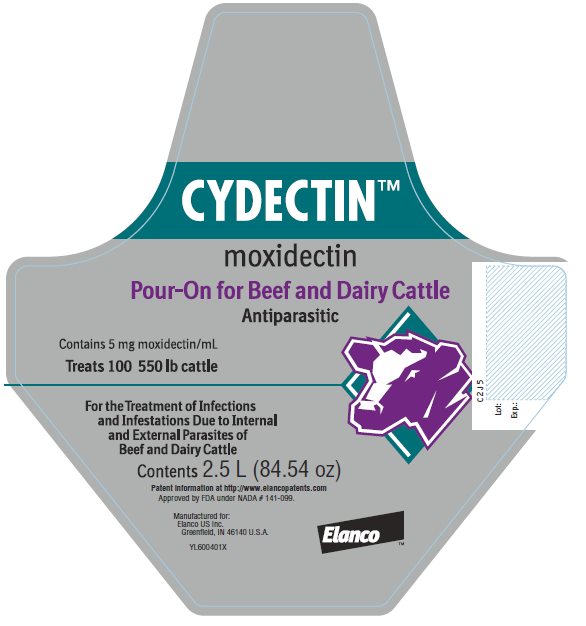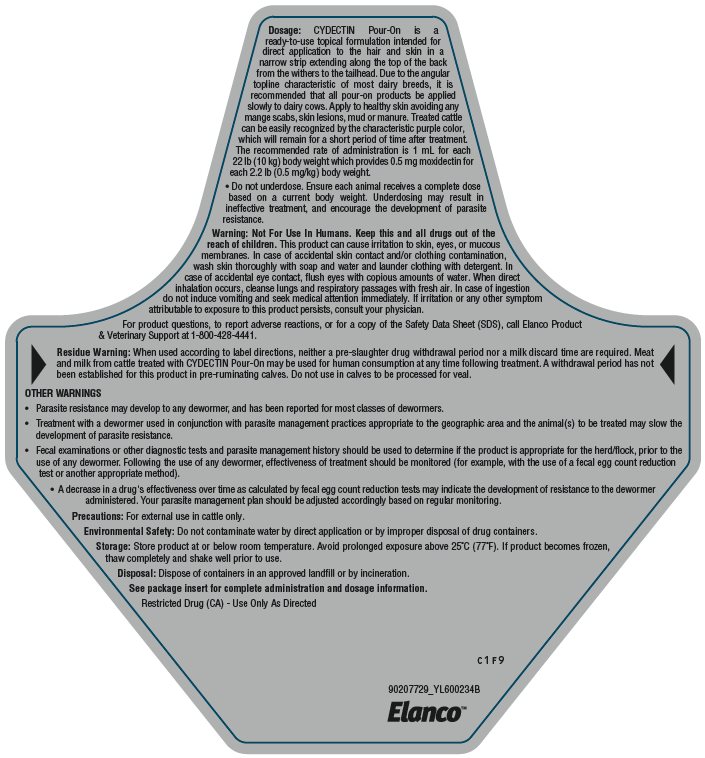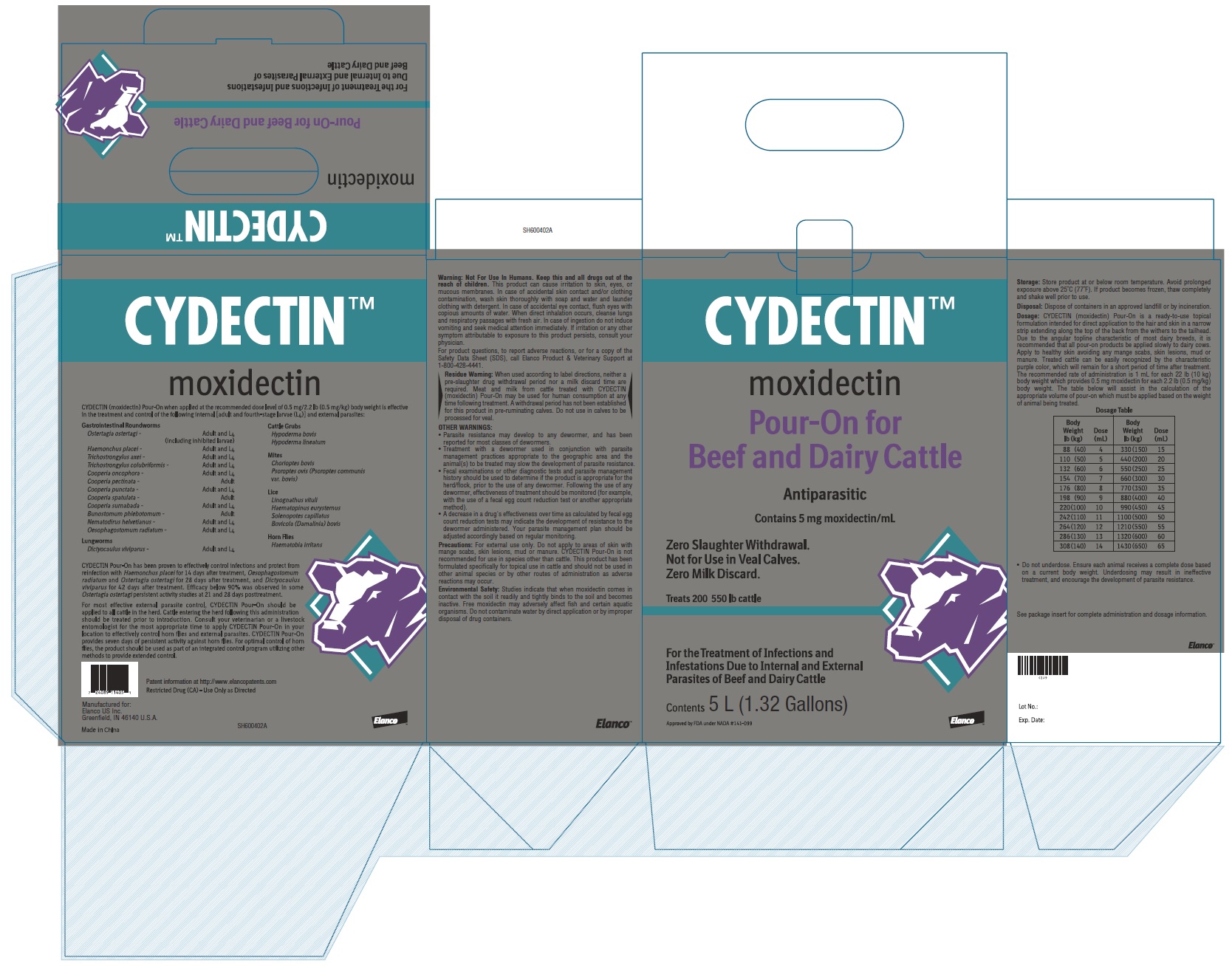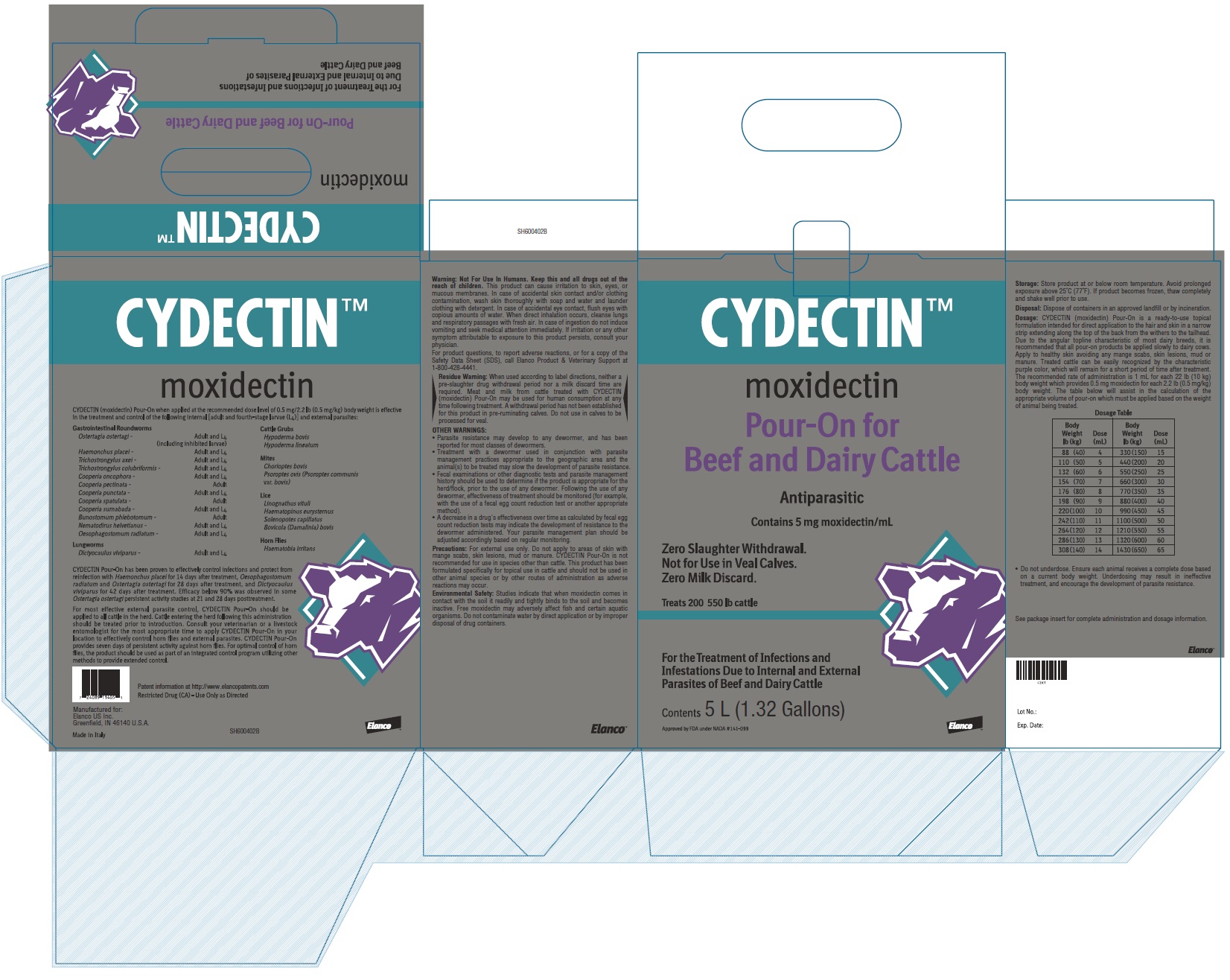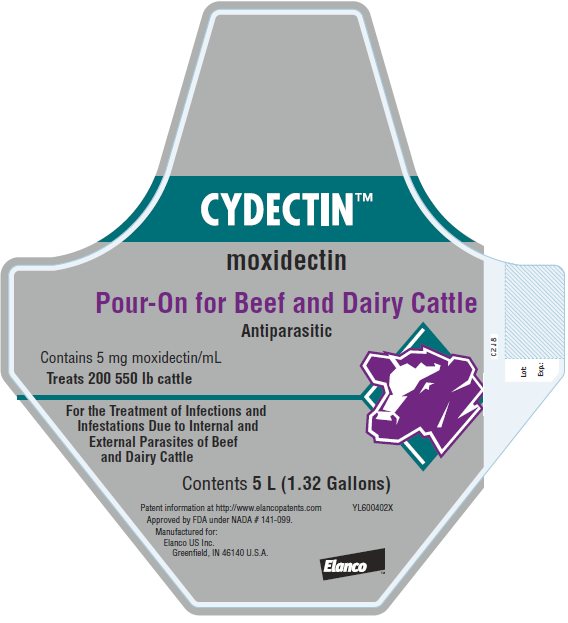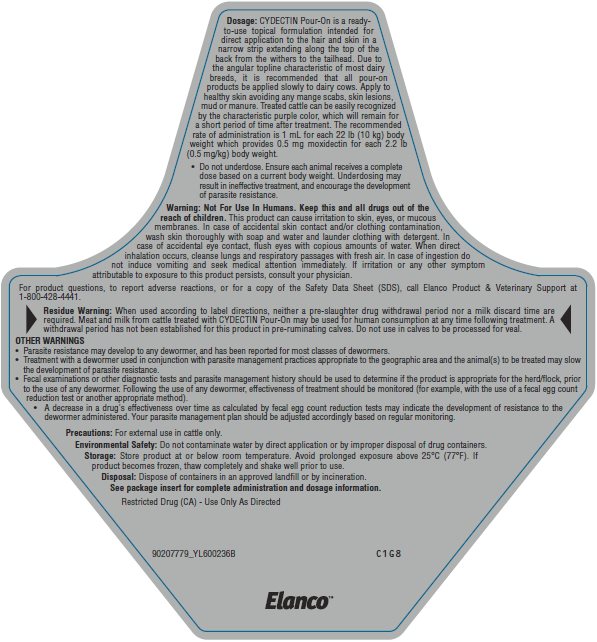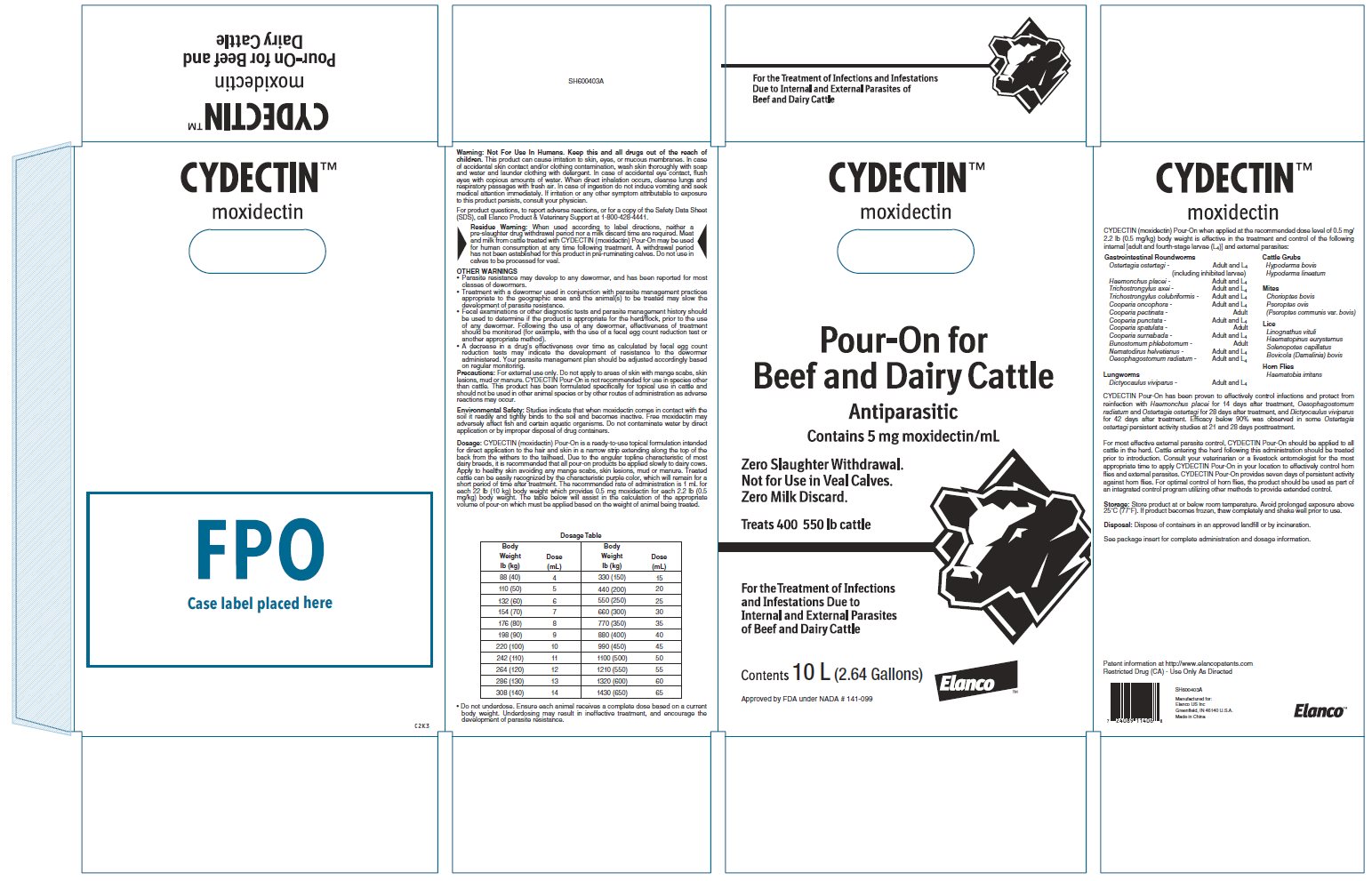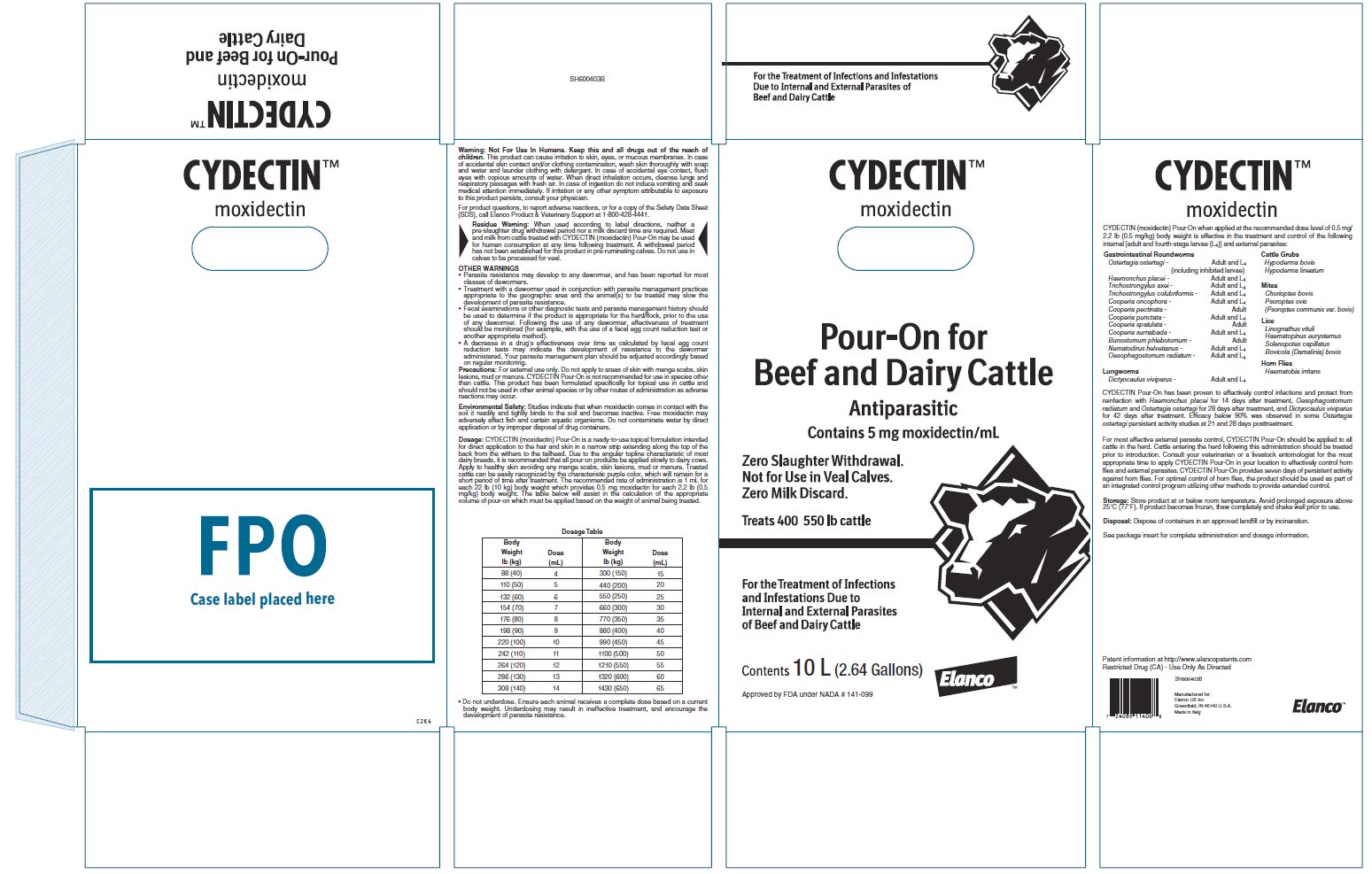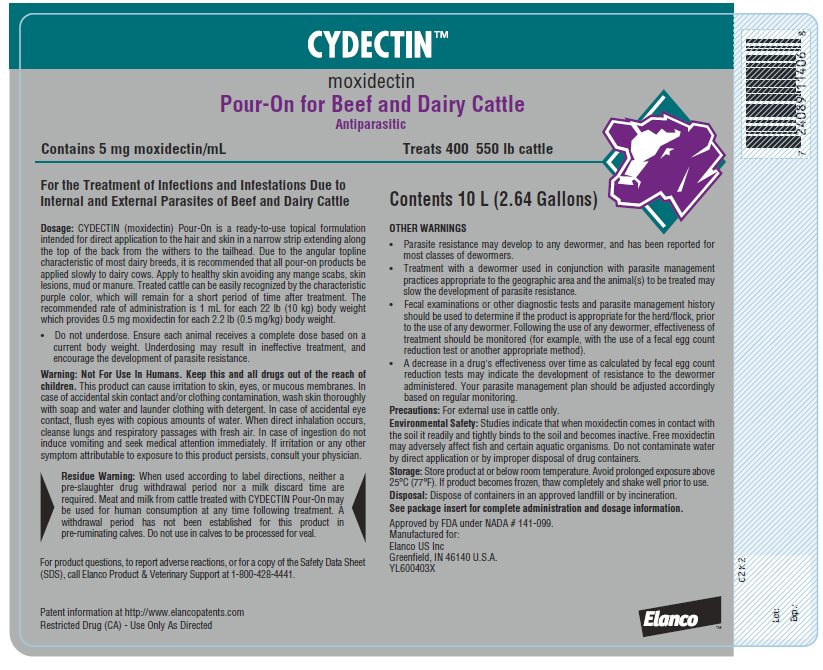 DRUG LABEL: Cydectin
NDC: 58198-0030 | Form: SOLUTION
Manufacturer: Elanco US Inc.
Category: animal | Type: OTC ANIMAL DRUG LABEL
Date: 20250124

ACTIVE INGREDIENTS: moxidectin 5 mg/1 mL

Approved by FDA under NADA # 141-099.

Elanco™

CYDECTIN™

moxidectin

Pour-On for Beef and Dairy Cattle

Antiparasitic

Contains 5 mg moxidectin/mL

For Treatment of Infections and Infestations Due to Internal and External Parasites of Beef and Dairy Cattle

Consult your veterinarian for assistance in the diagnosis, treatment and control of parasitism. If animals are likely to be reinfected following treatment, a strategic parasite control program should be established.

Mode of Action:

Moxidectin is an endectocide in the milbemycin chemical class which shares the distinctive mode of action characteristic of macrocyclic lactones. CYDECTIN (moxidectin) Pour-On is specially formulated to allow moxidectin to be absorbed through the skin and distributed internally to the areas of the body affected by endo- and/or ectoparasitism. Moxidectin binds selectively and with high affinity to glutamate-gated chloride ion channels which are critical to the function of invertebrate nerve and muscle cells. This interferes with neurotransmission resulting in paralysis and elimination of the parasite.

Indications:

CYDECTIN Pour-On when applied at the recommended dose level of 0.5 mg/2.2 lb (0.5 mg/kg) body weight is effective in the treatment and control of the following internal [adult and fourth-stage larvae (L4)] and external parasites of cattle:

Gastrointestinal Roundworms

Ostertagia ostertagi - Adult and L4 (including inhibited larvae)
Haemonchus placei - Adult and L4
Trichostrongylus axei - Adult and L4
Trichostrongylus colubriformis - Adult and L4
Cooperia oncophora - Adult and L4
Cooperia pectinata - Adult
Cooperia punctata - Adult and L4
Cooperia spatulata - Adult
Cooperia surnabada - Adult and L4
Bunostomum phlebotomum - Adult
Nematodirus helvetianus - Adult and L4
Oesophagostomum radiatum - Adult and L4

Lungworms

Dictyocaulus viviparus - Adult and L4

Cattle Grubs

Hypoderma bovis
Hypoderma lineatum

Mites

Chorioptes bovis
Psoroptes ovis (Psoroptes communis var. bovis)

Lice

Linognathus vituli
Haematopinus eurysternus
Solenopotes capillatus
Bovicola (Damalinia) bovis

Horn Flies

Haematobia irritans

Management Considerations for External Parasites:

For most effective external parasite control, CYDECTIN Pour-On should be applied to all cattle in the herd. Cattle entering the herd following this administration should be treated prior to introduction. Consult your veterinarian or a livestock entomologist for the most appropriate time to apply CYDECTIN Pour-On in your location to effectively control horn flies and external parasites. CYDECTIN Pour-On provides seven days of persistent activity against horn flies. For optimal control of horn flies, the product should be used as part of an integrated control program utilizing other methods to provide extended control.

Persistent Activity:

CYDECTIN Pour-On has been proven to effectively control infections and protect from reinfection with Haemonchus placei for 14 days after treatment, Oesophagostomum radiatum and Ostertagia ostertagi for 28 days after treatment, and Dictyocaulus viviparus for 42 days after treatment. Efficacy below 90% was observed in some Ostertagia ostertagi persistent activity studies at 21 and 28 days posttreatment.

Dosage:

CYDECTIN (moxidectin) Pour-On is a ready-to-use topical formulation intended for direct application to the hair and skin in a narrow strip extending along the top of the back from the withers to the tailhead (see Figure 1). Due to the angular topline characteristic of most dairy breeds, it is recommended that all pour‑on products be applied slowly to dairy cows. Apply to healthy skin avoiding any mange scabs, skin lesions, mud or manure. Treated cattle can be easily recognized by the characteristic purple color, which will remain for a short period of time after treatment. The recommended rate of administration is 1 mL for each 22 lb (10 kg) body weight which provides 0.5 mg moxidectin for each 2.2 lb (0.5 mg/kg) body weight. The table below will assist in the calculation of the appropriate volume of pour-on which must be applied based on the weight of animal being treated.

Body Weight Lb (kg) | Dose mL | Body Weight Lb (kg) | Dose mL
88 (40) | 4 | 330 (150) | 15
110 (50) | 5 | 440 (200) | 20
132 (60) | 6 | 550 (250) | 25
154 (70) | 7 | 660 (300) | 30
176 (80) | 8 | 770 (350) | 35
198 (90) | 9 | 880 (400) | 40
220 (100) | 10 | 990 (450) | 45
242 (110) | 11 | 1100 (500) | 50
264 (120) | 12 | 1210 (550) | 55
286 (130) | 13 | 1320 (600) | 60
308 (140) | 14 | 1430 (650) | 65

- Do not underdose. Ensure each animal receives a complete dose based on a current body weight. Underdosing may result in ineffective treatment, and encourage the development of parasite resistance.

Figure 1. Where to Apply CYDECTIN Pour-On

Use Conditions:

Varying weather conditions, including rainfall, do not affect the efficacy of CYDECTIN Pour-On.

Administration:

CYDECTIN Pour-On is available in three convenient package styles designed for ease of administration and the number of cattle to be treated. Directions for use of each container type follow:

Squeeze-Measure-Pour System (16.91 fl oz/500 mL and 33.81 fl oz/1 L Bottles)

Determine the weight of the animal, calculate the recommended volume of CYDECTIN Pour-On and locate the volume marker equivalent to this dose on the dosing chamber of the bottle. Remove the dosing chamber cap and squeeze the main chamber of bottle until the desired level of solution is present in the dosing chamber. Release pressure on the container to avoid further filling. Holding the dosing chamber as shown below, pour this measured volume of solution evenly along the backline of the animal from the withers to the tailhead (see Figure 1).

Figure 2. Squeeze-Measure-Pour System (16.91 fl oz/500 mL and 33.81 fl oz/1 L Bottles)

Large Conventional Containers (84.54 fl oz/2.5 L and 169 fl oz/5 L Bottles and 338 fl oz/10 L Cubetainer)

These bottles are designed for use with the CYDECTIN (moxidectin) Pour-On applicators. Simply remove the transient cap and seal and replace with the vented cap. Attach the applicator feeder hose to the vented cap. Invert the container prior to use (2.5 L and 5 L containers only). Apply the recommended volume of CYDECTIN Pour-On evenly along the backline of the animal from the withers to the tailhead (see Figure 1).

Figure 3. Large Conventional Containers (84.54 fl oz/2.5 L and 169 fl oz/5 L Bottles)
Figure 4. Large Conventional Container (338 fl oz/10 L Cubetainer)

Animal Safety:

Tolerance and toxicity studies have demonstrated an adequate margin of safety to allow treatment of cattle of all ages with CYDECTIN Pour-On. No toxic signs were seen in cattle given up to 25 times the recommended dose level. Newborn calves similarly showed no toxic signs when treated with up to three times the recommended dose level within 12 hours of birth and nursing from cows concurrently treated with the recommended dose level of CYDECTIN Pour-On. In breeding animals (bulls and cows in estrous and during early, mid and late pregnancy), treatment with three times the recommended dose level had no effect on breeding performance.

Warning:

Not For Use In Humans. Keep this and all drugs out of the reach of children. This product can cause irritation to skin, eyes, or mucous membranes. In case of accidental skin contact and/or clothing contamination, wash skin thoroughly with soap and water and launder clothing with detergent. In case of accidental eye contact, flush eyes with copious amounts of water. When direct inhalation occurs, cleanse lungs and respiratory passages with fresh air. In case of ingestion do not induce vomiting and seek medical attention immediately. If irritation or any other symptom attributable to exposure to this product persists, consult your physician.

For product questions, to report adverse reactions, or for a copy of the Safety Data Sheet (SDS), call Elanco Product & Veterinary Support at 1-800-428-4441.

Residue Warning:

When used according to label directions, neither a pre-slaughter drug withdrawal period nor a milk discard time are required. Meat and milk from cattle treated with CYDECTIN (moxidectin) Pour-On may be used for human consumption at any time following treatment. A withdrawal period has not been established for this product in preruminating calves. Do not use in calves to be processed for veal.

OTHER WARNINGS

- Parasite resistance may develop to any dewormer, and has been reported for most classes of dewormers.
- Treatment with a dewormer used in conjunction with parasite management practices appropriate to the geographic area and the animal(s) to be treated may slow the development of parasite resistance.
- Fecal examinations or other diagnostic tests and parasite management history should be used to determine if the product is appropriate for the herd/flock, prior to the use of any dewormer. Following the use of any dewormer, effectiveness of treatment should be monitored (for example, with the use of a fecal egg count reduction test or another appropriate method).
- A decrease in a drug's effectiveness over time as calculated by fecal egg count reduction tests may indicate the development of resistance to the dewormer administered. Your parasite management plan should be adjusted accordingly based on regular monitoring.

Precautions:

For external use only. Do not apply to areas of skin with mange scabs, skin lesions, mud or manure. CYDECTIN Pour-On is not recommended for use in species other than cattle. This product has been formulated specifically for topical use in cattle and should not be used in other animal species or by other routes of administration as adverse reactions may occur.

CYDECTIN Pour-On is effective against the migrating stage of cattle grubs (Hypoderma larvae). Treatment with CYDECTIN Pour-On during the period when grubs are migrating through vital areas may cause undesirable host-parasite reactions. Killing H. lineatum when they are located in periesophageal tissues may cause bloat. Killing H. bovis when they are in the vertebral canal may cause staggering or hindlimb paralysis. Cattle should be treated as soon as possible after heel fly (warble fly) season to avoid this potential problem. Cattle treated with CYDECTIN Pour-On at the end of fly season can be re-treated during the winter without danger of grub-related reactions. Consult your veterinarian for more information regarding these secondary grub reactions and the correct time to treat with CYDECTIN Pour‑On.

Environmental Safety:

Studies indicate that when moxidectin comes in contact with the soil it readily and tightly binds to the soil and becomes inactive. Free moxidectin may adversely affect fish and certain aquatic organisms. Do not contaminate water by direct application or by improper disposal of drug containers.

Storage:

Store product at or below room temperature. Avoid prolonged exposure above 25°C (77°F). If product becomes frozen, thaw completely and shake well prior to use.

Disposal:

Dispose of containers in an approved landfill or by incineration.

Package Information:

CYDECTIN Pour-On is available in five convenient container sizes. The 16.91 fl oz/500 mL and 33.81 fl oz/1 L are packaged in specially-designed squeeze-measure-pour polyethylene bottles. When treating larger numbers of cattle, 84.54 fl oz/2.5 L, 169 fl oz/5 L or 338 fl oz/10 L conventional polyethylene containers are available for use with most commercially-available topical applicators.

Patent information at http://www.elancopatents.com

Cydectin, Elanco and the diagonal bar logo are trademarks of Elanco or its affiliates
© 2022 Elanco or its affiliates.

Restricted Drug (CA) - Use Only As Directed
Revised: April 2022
90207956_PA600232X

Elanco™

Principal Display Panel - 500 mL Labels

CYDECTIN™
moxidectin

Pour-On for Beef
and Dairy Cattle

Antiparasitic

Contains 5 mg moxidectin/mL

Zero Slaughter Withdrawal.
Not for Use in Veal Calves.
Zero Milk Discard.

Treats 20 550 lb cattle

For the Treatment of Infections
and Infestations Due to
Internal and External
Parasites of Beef and
Dairy Cattle

Contents 500 mL (16.91 oz)

Approved by FDA under NADA # 141-099

Elanco

CYDECTIN™
moxidectin

Pour-On for Beef
and Dairy Cattle

Antiparasitic

Contains 5 mg moxidectin/mL

Zero Slaughter Withdrawal.
Not for Use in Veal Calves.
Zero Milk Discard.

Treats 20 550 lb cattle

For the Treatment of Infections
and Infestations Due to
Internal and External
Parasites of Beef and
Dairy Cattle

Contents 500 mL (16.91 oz)

Approved by FDA under NADA # 141-099

Elanco

CYDECTIN™
moxidectin

Pour-On for Beef
and Dairy Cattle

Antiparasitic

Contains 5 mg moxidectin/mL

Treats 20 550 lb cattle

Contents 500 mL (16.91 oz)

Patent information at
http://www.elancopatents.com

Approved by FDA under
NADA # 141-099.

Manufactured for:
Elanco US Inc.
Greenfield, IN 46140 U.S.A.

YL600399X

Restricted Drug (CA) - Use Only As Directed

See package insert for complete
administration and dosage information.

Elanco

Principal Display Panel - 1 L Labels

CYDECTIN™
moxidectin

Pour-On for Beef
and Dairy Cattle

Antiparasitic

Contains 5 mg moxidectin/mL

Zero Slaughter Withdrawal.
Not for Use in Veal Calves.
Zero Milk Discard.

Treats 40 550 lb cattle

For the Treatment of Infections
and Infestations Due to
Internal and External
Parasites of Beef and
Dairy Cattle

Contents 1 L (33.81 oz)

Approved by FDA under NADA # 141-099

Elanco™

CYDECTIN™
moxidectin

Pour-On for Beef
and Dairy Cattle

Antiparasitic

Contains 5 mg moxidectin/mL

Zero Slaughter Withdrawal.
Not for Use in Veal Calves.
Zero Milk Discard.

Treats 40 550 lb cattle

For the Treatment of Infections
and Infestations Due to
Internal and External
Parasites of Beef and
Dairy Cattle

Contents 1 L (33.81 oz)

Approved by FDA under NADA # 141-099

Elanco™

CYDECTIN™
moxidectin

Pour-On for Beef and Dairy Cattle

Antiparasitic

Contains 5 mg moxidectin/mL

Treats 40 550 lb cattle

For the Treatment of Infections and
Infestations Due to Internal and External
Parasites of Beef and Dairy Cattle

Patent information at http://www.elancopatents.com

Approved by FDA under NADA # 141-099.

Contents
1 L (33.81 oz)

Manufactured for:
Elanco US Inc.
Greenfield, IN 46140 U.S.A.

YL600400X

Elanco™

Principal Display Panel - 2.5 L Labels

CYDECTIN™
moxidectin

Pour-On for Beef
and Dairy Cattle

Antiparasitic

Contains 5 mg moxidectin/mL

Zero Slaughter Withdrawal.
Not for Use in Veal Calves.
Zero Milk Discard.

Treats 100 550 lb cattle

For the Treatment of Infections and
Infestations Due to Internal and External
Parasites of Beef and Dairy Cattle

Contents 2.5 L (84.54 oz)

Approved by FDA under NADA # 141-099

Elanco™

CYDECTIN™
moxidectin

Pour-On for Beef
and Dairy Cattle

Antiparasitic

Contains 5 mg moxidectin/mL

Zero Slaughter Withdrawal.
Not for Use in Veal Calves.
Zero Milk Discard.

Treats 100 550 lb cattle

For the Treatment of Infections and
Infestations Due to Internal and External
Parasites of Beef and Dairy Cattle

Contents 2.5 L (84.54 oz)

Approved by FDA under NADA # 141-099

Elanco™

CYDECTIN™
moxidectin

Pour-On for Beef and Dairy Cattle

Antiparasitic

Contains 5 mg moxidectin/mL

Treats 100 550 lb cattle

For the Treatment of Infections
and Infestations Due to Internal
and External Parasites of
Beef and Dairy Cattle

Contents 2.5 L (84.54 oz)

Patent information at http://www.elancopatents.com

Approved by FDA under NADA # 141-099.

Manufactured for:
Elanco US Inc.
Greenfield, IN 46140 U.S.A.

YL600401X

Elanco™

Principal Display Panel - 5 L Labels

CYDECTIN™
moxidectin

Pour-On for
Beef and Dairy Cattle

Antiparasitic

Contains 5 mg moxidectin/mL

Zero Slaughter Withdrawal.
Not for Use in Veal Calves.
Zero Milk Discard.

Treats 200 550 lb cattle

For the Treatment of Infections and
Infestations Due to Internal and External
Parasites of Beef and Dairy Cattle

Contents 5 L (1.32 Gallons)

Approved by FDA under NADA # 141-099

Elanco™

CYDECTIN™
moxidectin

Pour-On for
Beef and Dairy Cattle

Antiparasitic

Contains 5 mg moxidectin/mL

Zero Slaughter Withdrawal.
Not for Use in Veal Calves.
Zero Milk Discard.

Treats 200 550 lb cattle

For the Treatment of Infections and
Infestations Due to Internal and External
Parasites of Beef and Dairy Cattle

Contents 5 L (1.32 Gallons)

Approved by FDA under NADA # 141-099

Elanco™

CYDECTIN™
moxidectin

Pour-On for Beef and Dairy Cattle

Antiparasitic

Contains 5 mg moxidectin/mL

Treats 200 550 lb cattle

For the Treatment of Infections and
Infestations Due to Internal and
External Parasites of Beef
and Dairy Cattle

Contents 5 L (1.32 Gallons)

Patent information at http://www.elancopatents.com

Approved by FDA under NADA # 141-099.

Manufactured for:
Elanco US Inc.
Greenfield, IN 46140 U.S.A.

YL600402X

Elanco™

Principal Display Panel - 10 L Labels

CYDECTIN™
moxidectin

Pour-On for
Beef and Dairy Cattle

Antiparasitic

Contains 5 mg moxidectin/mL

Zero Slaughter Withdrawal.
Not for Use in Veal Calves.
Zero Milk Discard.

Treats 400 550 lb cattle

For the Treatment of Infections
and Infestations Due to
Internal and External Parasites
of Beef and Dairy Cattle

Contents 10 L (2.64 Gallons)

Approved by FDA under NADA # 141-099

Elanco™

CYDECTIN™
moxidectin

Pour-On for
Beef and Dairy Cattle

Antiparasitic

Contains 5 mg moxidectin/mL

Zero Slaughter Withdrawal.
Not for Use in Veal Calves.
Zero Milk Discard.

Treats 400 550 lb cattle

For the Treatment of Infections
and Infestations Due to
Internal and External Parasites
of Beef and Dairy Cattle

Contents 10 L (2.64 Gallons)

Approved by FDA under NADA # 141-099

Elanco™

CYDECTIN™
moxidectin

Pour-On for Beef and Dairy Cattle

Antiparasitic

Contains 5 mg moxidectin/mL

Treats 400 550 lb cattle

For the Treatment of Infections and Infestations Due to
Internal and External Parasites of Beef and Dairy Cattle

Contents 10 L (2.64 Gallons)

Patent information at http://www.elancopatents.com

Restricted Drug (CA) - Use Only As Directed

Approved by FDA under NADA # 141-099.

Manufactured for:
Elanco US Inc
Greenfield, IN 46140 U.S.A.

YL600403X

Elanco™